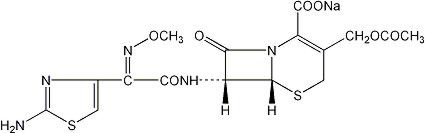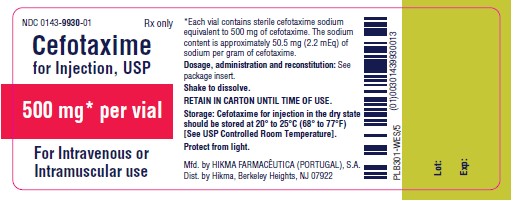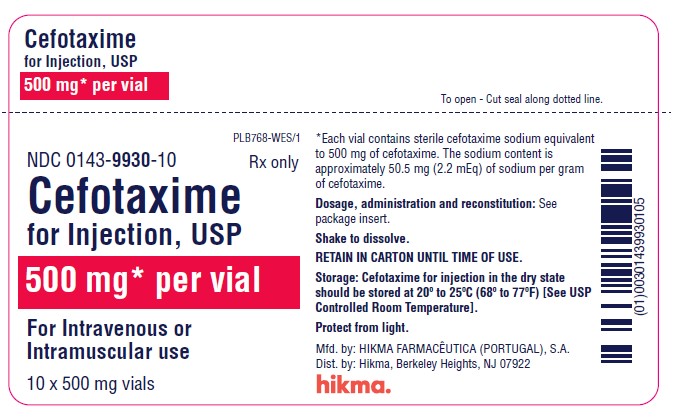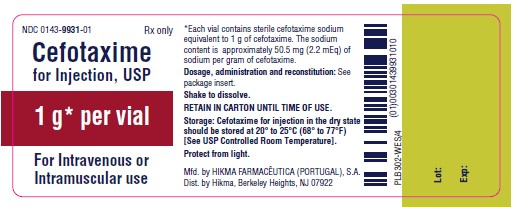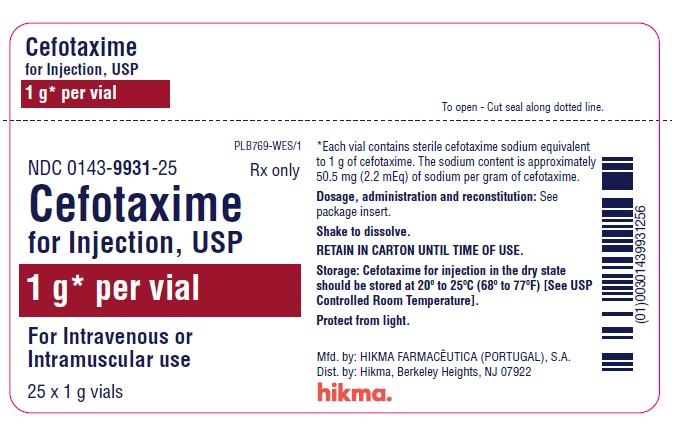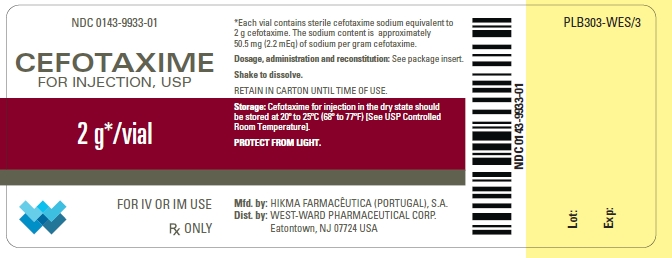 DRUG LABEL: Cefotaxime
NDC: 0143-9931 | Form: INJECTION, POWDER, FOR SOLUTION
Manufacturer: Hikma Pharmaceuticals USA Inc.
Category: prescription | Type: HUMAN PRESCRIPTION DRUG LABEL
Date: 20240411

ACTIVE INGREDIENTS: CEFOTAXIME SODIUM 1 g/1 1

CEFOTAXIME FOR INJECTION, USP

Rx ONLY

To reduce the development of drug-resistant bacteria and maintain the effectiveness of Cefotaxime for Injection, USP (cefotaxime sodium) and other antibacterial drugs, Cefotaxime for Injection, USP should be used only to treat or prevent infections that are proven or strongly suspected to be caused by bacteria.

DESCRIPTION

Sterile cefotaxime sodium is a semisynthetic, broad spectrum cephalosporin antibiotic for parenteral administration. It is the sodium salt of 7-[2-(2-amino-4-thiazolyl) glyoxylamido]-3(hydroxymethyl)-8-oxo-5-thia-1-azabicyclo [4.2.0] oct-2-ene-2-carboxylate 72 (Z)-(o-methyloxime), acetate (ester). Cefotaxime for Injection, USP contains approximately 50.5 mg (2.2 mEq) of sodium per gram of cefotaxime activity. Solutions of Cefotaxime for Injection, USP range from very pale yellow to light amber depending on the concentration and the diluent used. The pH of the injectable solutions usually ranges from 5.0 to 7.5. The CAS Registry Number is 64485-93-4.

C16H16N5NaO7S2 MW 477.45

Cefotaxime for Injection, USP is supplied as a dry powder in vials. Each vial contains cefotaxime sodium, equivalent to 500 mg, 1 gram or 2 grams of cefotaxime.

CLINICAL PHARMACOLOGY

Following IM administration of a single 500 mg or 1 g dose of cefotaxime to normal volunteers, mean peak serum concentrations of 11.7 and 20.5 mcg/mL respectively were attained within 30 minutes and declined with an elimination half-life of approximately 1 hour. There was a dose-dependent increase in serum levels after the IV administration of 500 mg, 1 g, and 2 g of cefotaxime (38.9, 101.7, and 214.4 mcg/mL respectively) without alteration in the elimination half-life. There is no evidence of accumulation following repetitive IV infusion of 1 g doses every 6 hours for 14 days as there are no alterations of serum or renal clearance. About 60% of the administered dose was recovered from urine during the first 6 hours following the start of the infusion.

Approximately 20-36% of an intravenously administered dose of ^14C-cefotaxime is excreted by the kidney as unchanged cefotaxime and 15-25% as the desacetyl derivative, the major metabolite. The desacetyl metabolite has been shown to contribute to the bactericidal activity. Two other urinary metabolites (M2 and M3) account for about 20-25%. They lack bactericidal activity.

A single 50 mg/kg dose of cefotaxime was administered as an intravenous infusion over a 10- to 15-minute period to 29 newborn infants grouped according to birth weight and age. The mean half-life of cefotaxime in infants with lower birth weights (≤ 1500 grams), regardless of age, was longer (4.6 hours) than the mean half-life (3.4 hours) in infants whose birth weight was greater than 1500 grams. Mean serum clearance was also smaller in the lower birth weight infants. Although the differences in mean half-life values are statistically significant for weight, they are not clinically important. Therefore, dosage should be based solely on age. (See DOSAGE AND ADMINISTRATION section.)

Drug Interactions

A single intravenous dose and oral dose of probenecid (500 mg each) followed by two oral doses of probenecid 500 mg at approximately hourly intervals administered to three healthy male subjects receiving a continuous infusion of cefotaxime increased the steady-state plasma concentration of cefotaxime by approximately 80%. In another study, administration of oral probenecid 500 mg every 6 hours to six healthy male subjects with cefotaxime 1 gram infused over 5 minutes decreased the total clearance of cefotaxime by approximately 50%.

Additionally, no disulfiram-like reactions were reported in a study conducted in 22 healthy volunteers administered cefotaxime and ethanol.

Microbiology

Mechanism of Action
Cefotaxime sodium is a bactericidal agent that acts by inhibition of bacterial cell wall synthesis. Cefotaxime has activity in the presence of some of beta-lactamases, both penicillinases and cephalosporinases, of Gram-negative and Gram-positive bacteria.

Mechanism of Resistance
Resistance to cefotaxime is primarily through hydrolysis by beta-lactamase, alteration of penicillin-binding proteins (PBPs), and decreased permeability.

Susceptibility to cefotaxime will vary geographically and may change over time; local susceptibility data should be consulted, if available. Cefotaxime has been shown to be active against most isolates of the following bacteria both in vitro and in clinical infections as described in the INDICATIONS AND USAGE section:

Gram-positive bacteria
Enterococcus spp. a
Staphylococcus aureus (methicillin-susceptible isolates only)
Staphylococcus epidermidis
Streptococcus pneumoniae
Streptococcus pyogenes (Group A beta-hemolytic streptococci)
Streptococcus spp. (Viridans group streptococci)

Gram-negative bacteria
Acinetobacter spp.
Citrobacter spp.b
Enterobacter spp. b
Escherichia coli b
Haemophilus influenzae
Haemophilus parainfluenzae
Klebsiella spp. (including Klebsiella pneumoniae) b
Morganella morganii b
Neisseria gonorrhoeae (including beta-lactamase-positive and negative strains)
Neisseria meningitidis
Proteus mirabilis b
Proteus vulgaris b
Providencia rettgeri b
Providencia stuartii b
Serratia marcescens b

a Enterococcus species may be intrinsically resistant to cefotaxime.
b Most extended spectrum beta-lactamase (ESBL)-producing and carbapenemase-producing isolates are resistant to cefotaxime.

Anaerobic bacteria
Bacteroides spp., including some isolates of Bacteroides fragilis
Clostridium spp. (most isolates of Clostridium difficile are resistant)
Fusobacterium spp. (including Fusobacterium nucleatum).
Peptococcus spp.
Peptostreptococcus spp.

The following in vitro data are available, but their clinical significance is unknown. At least 90 percent of the following microorganisms exhibit an in vitro minimum inhibitory concentration (MIC) less than or equal to 1 mcg/mL. However, the efficacy of cefotaxime in treating clinical infections due to these microorganisms has not been established in adequate and well-controlled clinical trials.

Gram-negative bacteria
Providencia spp.
Salmonella spp. (including Salmonella typhi)
Shigella spp.

Susceptibility Test Methods

For specific information regarding susceptibility test interpretive criteria and associated test methods and quality control standards recognized by FDA for this drug, please see: https://www.fda.gov/STIC.

INDICATIONS AND USAGE

Treatment

Cefotaxime for Injection, USP is indicated for the treatment of patients with serious infections caused by susceptible strains of the designated microorganisms in the diseases listed below.

(1) Lower respiratory tract infections, including pneumonia, caused by Streptococcus pneumoniae (formerly Diplococcus pneumoniae), Streptococcus pyogenes* (Group A streptococci) and other streptococci (excluding enterococci, e.g., Enterococcus faecalis), Staphylococcus aureus (penicillinase and non-penicillinase producing), Escherichia coli, Klebsiella species, Haemophilus influenzae (including ampicillin resistant strains), Haemophilus parainfluenzae, Proteus mirabilis, Serratia marcescens*, Enterobacter species, indole positive Proteus and Pseudomonas species (including P. aeruginosa).

(2) Genitourinary infections. Urinary tract infections caused by Enterococcus species, Staphylococcus epidermidis, Staphylococcus aureus*, (penicillinase and non-penicillinase producing), Citrobacter species, Enterobacter species, Escherichia coli, Klebsiella species, Proteus mirabilis, Proteus vulgaris*, Providencia stuartii, Morganella morganii*, Providencia rettgeri*, Serratia marcescens and Pseudomonas species (including P. aeruginosa). Also, uncomplicated gonorrhea (cervical/urethral and rectal) caused by Neisseria gonorrhoeae, including penicillinase producing strains.

(3) Gynecologic infections, including pelvic inflammatory disease, endometritis and pelvic cellulitis caused by Staphylococcus epidermidis, Streptococcus species, Enterococcus species, Enterobacter species*, Klebsiella species*, Escherichia coli, Proteus mirabilis, Bacteroides species (including Bacteroides fragilis*), Clostridium species, and anaerobic cocci (including Peptostreptococcus species and Peptococcus species) and Fusobacterium species (including F. nucleatum*).
Cefotaxime for Injection, USP, like other cephalosporins, has no activity against Chlamydia trachomatis. Therefore, when cephalosporins are used in the treatment of patients with pelvic inflammatory disease and C. trachomatis is one of the suspected pathogens, appropriate anti-chlamydial coverage should be added.

(4) Bacteremia/Septicemia caused by Escherichia coli, Klebsiella species, and Serratia marcescens, Staphylococcus aureus and Streptococcus species (including S. pneumoniae).

(5) Skin and skin structure infections caused by Staphylococcus aureus (penicillinase and non-penicillinase producing), Staphylococcus epidermidis, Streptococcus pyogenes (Group A streptococci) and other streptococci, Enterococcus species, Acinetobacter species*, Escherichia coli, Citrobacter species (including C. freundii*), Enterobacter species, Klebsiella species, Proteus mirabilis, Proteus vulgaris*, Morganella morganii, Providencia rettgeri*, Pseudomonas species, Serratia marcescens, Bacteroides species, and anaerobic cocci (including Peptostreptococcus* species and Peptococcus species).

(6) Intra-abdominal infections including peritonitis caused by Streptococcus species*, Escherichia coli, Klebsiella species, Bacteroides species, and anaerobic cocci (including Peptostreptococcus* species and Peptococcus* species) Proteus mirabilis*, and Clostridium species*.

(7) Bone and/or joint infections caused by Staphylococcus aureus (penicillinase and non-penicillinase producing strains), Streptococcus species (including S. pyogenes*), Pseudomonas species (including P. aeruginosa*), and Proteus mirabilis*.

(8) Central nervous system infections, e.g., meningitis and ventriculitis, caused by Neisseria meningitidis, Haemophilus influenzae, Streptococcus pneumoniae, Klebsiella pneumoniae* and Escherichia coli*.

(*) Efficacy for this organism, in this organ system, has been studied in fewer than 10 infections.

Although many strains of enterococci (e.g., S. faecalis) and Pseudomonas species are resistant to cefotaxime sodium in vitro, Cefotaxime for Injection, USP has been used successfully in treating patients with infections caused by susceptible organisms.

Specimens for bacteriologic culture should be obtained prior to therapy in order to isolate and identify causative organisms and to determine their susceptibilities to cefotaxime. Therapy may be instituted before results of susceptibility studies are known; however, once these results become available, the antibiotic treatment should be adjusted accordingly.

In certain cases of confirmed or suspected gram-positive or gram-negative sepsis or in patients with other serious infections in which the causative organism has not been identified, Cefotaxime for Injection, USP may be used concomitantly with an aminoglycoside. The dosage recommended in the labeling of both antibiotics may be given and depends on the severity of the infection and the patient's condition. Renal function should be carefully monitored, especially if higher dosages of the aminoglycosides are to be administered or if therapy is prolonged, because of the potential nephrotoxicity and ototoxicity of aminoglycoside antibiotics. It is possible that nephrotoxicity may be potentiated if Cefotaxime for Injection, USP is used concomitantly with an aminoglycoside.

Prevention

The administration of Cefotaxime for Injection, USP preoperatively reduces the incidence of certain infections in patients undergoing surgical procedures (e.g., abdominal or vaginal hysterectomy, gastrointestinal and genitourinary tract surgery) that may be classified as contaminated or potentially contaminated.

In patients undergoing cesarean section, intraoperative (after clamping the umbilical cord) and postoperative use of Cefotaxime for Injection, USP may also reduce the incidence of certain postoperative infections. See DOSAGE AND ADMINISTRATION section.

Effective use for elective surgery depends on the time of administration. To achieve effective tissue levels, Cefotaxime for Injection, USP should be given 1/2 or 1 1/2 hours before surgery. See DOSAGE AND ADMINISTRATION section.

For patients undergoing gastrointestinal surgery, preoperative bowel preparation by mechanical cleansing as well as with a non-absorbable antibiotic (e.g., neomycin) is recommended.

If there are signs of infection, specimens for culture should be obtained for identification of the causative organism so that appropriate therapy may be instituted.

To reduce the development of drug-resistant bacteria and maintain the effectiveness of Cefotaxime for Injection, USP and other antibacterial drugs, Cefotaxime for Injection, USP should be used only to treat or prevent infections that are proven or strongly suspected to be caused by susceptible bacteria. When culture and susceptibility information are available, they should be considered in selecting or modifying antibacterial therapy. In the absence of such data, local epidemiology and susceptibility patterns may contribute to the empiric selection of therapy.

CONTRAINDICATIONS

Cefotaxime is contraindicated in patients who have shown hypersensitivity to cefotaxime sodium, or the cephalosporin group of antibiotics.

WARNINGS

BEFORE THERAPY WITH CEFOTAXIME IS INSTITUTED, CAREFUL INQUIRY SHOULD BE MADE TO DETERMINE WHETHER THE PATIENT HAS HAD PREVIOUS HYPERSENSITIVITY REACTIONS TO CEFOTAXIME SODIUM, CEPHALOSPORINS, PENICILLINS, OR OTHER DRUGS. THIS PRODUCT SHOULD BE GIVEN WITH CAUTION TO PATIENTS WITH TYPE I HYPERSENSITIVITY REACTIONS TO PENICILLIN. ANTIBIOTICS SHOULD BE ADMINISTERED WITH CAUTION TO ANY PATIENT WHO HAS DEMONSTRATED SOME FORM OF ALLERGY, PARTICULARLY TO DRUGS. IF AN ALLERGIC REACTION TO CEFOTAXIME OCCURS, DISCONTINUE TREATMENT WITH THE DRUG. SERIOUS HYPERSENSITIVITY REACTIONS MAY REQUIRE EPINEPHRINE AND OTHER EMERGENCY MEASURES.

During post-marketing surveillance, a potentially life-threatening arrhythmia was reported in each of six patients who received a rapid (less than 60 seconds) bolus injection of cefotaxime through a central venous catheter. Therefore, cefotaxime should only be administered as instructed in the DOSAGE AND ADMINISTRATION section.

Clostridium difficile associated diarrhea (CDAD) has been reported with use of nearly all antibacterial agents, including cefotaxime, and may range in severity from mild diarrhea to fatal colitis. Treatment with antibacterial agents alters the normal flora of the colon leading to overgrowth of C. difficile.

C. difficile produces toxins A and B which contribute to the development of CDAD. Hypertoxin producing strains of C. difficile cause increased morbidity and mortality, as these infections can be refractory to antimicrobial therapy and may require colectomy. CDAD must be considered in all patients who present with diarrhea following antibiotic use. Careful medical history is necessary since CDAD has been reported to occur over two months after the administration of antibacterial agents.

If CDAD is suspected or confirmed, ongoing antibiotic use not directed against C. difficile may need to be discontinued. Appropriate fluid and electrolyte management, protein supplementation, antibiotic treatment of C. difficile, and surgical evaluation should be instituted as clinically indicated.

PRECAUTIONS

General

Prescribing cefotaxime in the absence of a proven or strongly suspected bacterial infection or a prophylactic indication is unlikely to provide benefit to the patient and increases the risk of the development of drug-resistant bacteria.

Cefotaxime should be prescribed with caution in individuals with a history of gastrointestinal disease, particularly colitis.

Because high and prolonged serum antibiotic concentrations can occur from usual doses in patients with transient or persistent reduction of urinary output because of renal insufficiency, the total daily dosage should be reduced when cefotaxime is administered to such patients. Continued dosage should be determined by degree of renal impairment, severity of infection, and susceptibility of the causative organism.

Although there is no clinical evidence supporting the necessity of changing the dosage of cefotaxime sodium in patients with even profound renal dysfunction, it is suggested that, until further data are obtained, the dose of cefotaxime sodium be halved in patients with estimated creatinine clearances of less than 20 mL/min/1.73 m^2.

When only serum creatinine is available, the following formula^5 (based on sex, weight, and age of the patient) may be used to convert this value into creatinine clearance. The serum creatinine should represent a steady state of renal function.

Males: Weight (kg) x (140 - age)
72 × serum creatinine

Females: 0.85 × above value

As with other antibiotics, prolonged use of cefotaxime may result in overgrowth of nonsusceptible organisms. Repeated evaluation of the patient's condition is essential. If superinfection occurs during therapy, appropriate measures should be taken.

Leukopenia, neutropenia, granulocytopenia and, more rarely, bone marrow failure, pancytopenia, or agranulocytosis may develop during treatment with cefotaxime. For courses of treatment lasting longer than 10 days, blood counts should therefore be monitored and treatment discontinuation should be considered in case of abnormal results.

Cefotaxime, like other parenteral anti-infective drugs, may be locally irritating to tissues. In most cases, perivascular extravasation of cefotaxime responds to changing of the infusion site. In rare instances, extensive perivascular extravasation of cefotaxime may result in tissue damage and require surgical treatment. To minimize the potential for tissue inflammation, infusion sites should be monitored regularly and changed when appropriate.

Information for patients

Patients should be counseled that antibacterial drugs including cefotaxime should only be used to treat bacterial infections. They do not treat viral infections (e.g., the common cold). When cefotaxime is prescribed to treat a bacterial infection, patients should be told that although it is common to feel better early in the course of therapy, the medication should be taken exactly as directed. Skipping doses or not completing the full course of therapy may (1) decrease the effectiveness of the immediate treatment and (2) increase the likelihood that bacteria will develop resistance and will not be treatable by cefotaxime or other antibacterial drugs in the future.

Diarrhea is a common problem caused by antibiotics which usually ends when the antibiotic is discontinued. Sometimes after starting treatment with antibiotics, patients can develop watery and bloody stools (with or without stomach cramps and fever) even as late as two or more months after having taken the last dose of the antibiotic. If this occurs, patients should contact their physician as soon as possible.

Drug Interactions

As with other cephalosporins, cefotaxime may potentiate the nephrotoxic effects of nephrotoxic drugs such as aminoglycosides, NSAIDs and furosemide.

Probenecid interferes with the renal tubular transfer of cefotaxime, decreasing the total clearance of cefotaxime by approximately 50% and increasing the plasma concentrations of cefotaxime. Administration of cefotaxime in excess of 6 grams/day should be avoided in patients receiving probenecid (see CLINICAL PHARMACOLOGY, Drug Interactions).

Drug/Laboratory Test Interactions

Cephalosporins, including cefotaxime sodium, are known to occasionally induce a positive direct Coombs' test.

A false-positive reaction for glucose in the urine may occur with copper reduction tests (Benedict's or Fehling's solution or with CLINITEST® tablets), but not with enzyme-based tests for glycosuria (e.g., CLINISTIX® or TesTape®). There are no reports in published literature that link elevations of plasma glucose levels to the use of cefotaxime.

Carcinogenesis, Mutagenesis

Lifetime studies in animals to evaluate carcinogenic potential have not been conducted. Cefotaxime was not mutagenic in the mouse micronucleus test or in the Ames test. Cefotaxime did not impair fertility to rats when administered subcutaneously at doses up to 250 mg/kg/day (0.2 times the maximum recommended human dose based on mg/m^2) or in mice when administered intravenously at doses up to 2000 mg/kg/day (0.7 times the recommended human dose based on mg/m^2).

Pregnancy: Teratogenic Effects

Reproduction studies have been performed in pregnant mice given cefotaxime intravenously at doses up to 1200 mg/kg/day (0.4 times the recommended human dose based on mg/m^2) or in pregnant rats when administered intravenously at doses up to 1200 mg/kg/day (0.8 times the recommended human dose based on mg/m^2). No evidence of embryotoxicity or teratogenicity was seen in these studies. Although cefotaxime has been reported to cross the placental barrier and appear in cord blood, the effect on the human fetus is not known. There are no well-controlled studies in pregnant women. Because animal reproductive studies are not always predictive of human response, this drug should be used during pregnancy only if clearly needed.

Nonteratogenic Effects

Use of the drug in women of child-bearing potential requires that the anticipated benefit be weighed against the possible risks.

In perinatal and postnatal studies with rats, the pups in the group given 1200 mg/kg/day of cefotaxime were significantly lighter in weight at birth and remained smaller than pups in the control group during the 21 days of nursing.

Nursing Mothers

Cefotaxime is excreted in human milk in low concentrations. Caution should be exercised when cefotaxime is administered to a nursing woman.

Pediatric Use

See PRECAUTIONS above regarding perivascular extravasation.

Geriatric Use

Of the 1409 subjects in clinical studies of cefotaxime, 632 (45%) were 65 and over, while 258 (18%) were 75 and over. No overall differences in safety or effectiveness were observed between these subjects and younger subjects, and other reported clinical experience has not identified differences in responses between the elderly and younger patients, but greater sensitivity of some older individuals cannot be ruled out.

This drug is known to be substantially excreted by the kidney, and the risk of toxic reactions to this drug may be greater in patients with impaired renal function. Because elderly patients are more likely to have decreased renal function, care should be taken in dose selection, and it may be useful to monitor renal function (see PRECAUTIONS, General).

ADVERSE REACTIONS

Clinical Trials Experience

Cefotaxime is generally well tolerated. The most common adverse reactions have been local reactions following IM or IV injection. Other adverse reactions have been encountered infrequently.

The most frequent adverse reactions (greater than 1%) are:
Local (4.3%) - Injection site inflammation with IV administration. Pain, induration, and tenderness after IM injection.
Hypersensitivity (2.4%) - Rash, pruritus, fever, eosinophilia.
Gastrointestinal (1.4%) - Colitis, diarrhea, nausea, and vomiting.
Symptoms of pseudomembranous colitis can appear during or after antibiotic treatment.
Nausea and vomiting have been reported rarely.

Less frequent adverse reactions (less than 1%) are:
Hematologic System - Neutropenia, leukopenia, have been reported. Some individuals have developed positive direct Coombs Tests during treatment with cefotaxime and other cephalosporin antibiotics.
Genitourinary System - Moniliasis, vaginitis.
Central Nervous System - Headache.
Liver - Transient elevations in AST, ALT, serum LDH, and serum alkaline phosphatase levels have been reported.
Kidney - As with some other cephalosporins, transient elevations of BUN have been occasionally observed with cefotaxime.

Post-Marketing Experience

The following adverse reactions have been identified during post-approval use of cefotaxime. Because these reactions were reported voluntarily from a population of uncertain size, it is not possible to reliably estimate their frequency or establish a causal relationship to drug exposure.

Cardiovascular System - Potentially life-threatening arrhythmias following rapid (less than 60 seconds) bolus administration via central venous catheter have been observed.

Central Nervous System - Administration of high doses of beta-lactam antibiotics, including cefotaxime, particularly in patients with renal insufficiency may result in encephalopathy (e.g. impairment of consciousness, abnormal movements and convulsions). Dizziness has also been reported.

Cutaneous - As with other cephalosporins, isolated cases of toxic epidermal necrolysis, Stevens-Johnson syndrome, and erythema multiforme have been reported. Acute generalized exanthematous pustulosis (AGEP) has also been reported.
General disorders and administration site conditions - Inflammatory reactions at the injection site, including phlebitis/thrombophlebitis.

Hematologic System - Hemolytic anemia, agranulocytosis, thrombocytopenia, pancytopenia, bone marrow failure.

Hypersensitivity - Anaphylaxis (e.g., angioedema, bronchospasm, malaise possibly culminating in shock), urticaria.

Kidney - Interstitial nephritis, transient elevations of creatinine, acute renal failure.

Liver - Hepatitis, jaundice, cholestasis, elevations of gamma GT and bilirubin.

Cephalosporin Class Labeling

In addition to the adverse reactions listed above which have been observed in patients treated with cefotaxime sodium, the following adverse reactions and altered laboratory tests have been reported for cephalosporin class antibiotics: allergic reactions, hepatic dysfunction including cholestasis, aplastic anemia, hemorrhage, and false-positive test for urinary glucose.

Several cephalosporins have been implicated in triggering seizures, particularly in patients with renal impairment when the dosage was not reduced. See DOSAGE AND ADMINISTRATION and OVERDOSAGE. If seizures associated with drug therapy occur, the drug should be discontinued. Anticonvulsant therapy can be given if clinically indicated.

To report SUSPECTED ADVERSE REACTIONS, contact Hikma Pharmaceuticals USA Inc. at 1-877-845-0689 or FDA at 1-800-FDA-1088 or www.fda.gov/medwatch.

OVERDOSAGE

The acute toxicity of cefotaxime was evaluated in neonatal and adult mice and rats. Significant mortality was seen at parenteral doses in excess of 6000 mg/kg/day in all groups. Common toxic signs in animals that died were a decrease in spontaneous activity, tonic and clonic convulsions, dyspnea, hypothermia, and cyanosis. Cefotaxime sodium overdosage has occurred in patients. Most cases have shown no overt toxicity. The most frequent reactions were elevations of BUN and creatinine. There is a risk of reversible encephalopathy in cases of administration of high doses of beta-lactam antibiotics including cefotaxime. No specific antidote exists. Patients who receive an acute overdosage should be carefully observed and given supportive treatment.

DOSAGE AND ADMINISTRATION

Adults

Dosage and route of administration should be determined by susceptibility of the causative organisms, severity of the infection, and the condition of the patient (see table for dosage guideline). Cefotaxime may be administered IM or IV after reconstitution. The maximum daily dosage should not exceed 12 grams.

GUIDELINES FOR DOSAGE OF CEFOTAXIME FOR INJECTION
Type of Infection | Daily Dose (grams) | Frequency and Route
Gonococcal urethritis/cervicitis in males and females | 0.5 | 0.5 gram IM (single dose)
Rectal gonorrhea in females | 0.5 | 0.5 gram IM (single dose)
Rectal gonorrhea in males | 1 | 1 gram IM (single dose)
Uncomplicated infections | 2 | 1 gram every 12 hours IM or IV
Moderate to severe infections | 3-6 | 1-2 grams every 8 hours IM or IV
Infections commonly needing antibiotics in higher dosage (e.g., septicemia) | 6-8 | 2 grams every 6-8 hours IV
Life-threatening infections | up to 12 | 2 grams every 4 hours IV

If C. trachomatis is a suspected pathogen, appropriate anti-chlamydial coverage should be added, because cefotaxime sodium has no activity against this organism.

To prevent postoperative infection in contaminated or potentially contaminated surgery, the recommended dose is a single 1 gram IM or IV administered 30 to 90 minutes prior to start of surgery.

Cesarean Section Patients

The first dose of 1 gram is administered intravenously as soon as the umbilical cord is clamped. The second and third doses should be given as 1 gram intravenously or intramuscularly at 6 and 12 hours after the first dose.

Neonates, Infants, and Children

The following dosage schedule is recommended:

Neonates (birth to 1 month):
0-1 week of age 50 mg/kg per dose every 12 hours IV
1-4 weeks of age 50 mg/kg per dose every 8 hours IV

It is not necessary to differentiate between premature and normal-gestational age infants.

Infants and Children (1 month to 12 years):
For body weights less than 50 kg, the recommended daily dose is 50 to 180 mg/kg IM or IV body weight divided into four to six equal doses. The higher dosages should be used for more severe or serious infections, including meningitis. For body weights 50 kg or more, the usual adult dosage should be used; the maximum daily dosage should not exceed 12 grams.

Geriatric Use

This drug is known to be substantially excreted by the kidney, and the risk of toxic reactions to this drug may be greater in patients with impaired renal function. Because elderly patients are more likely to have decreased renal function, care should be taken in dose selection, and it may be useful to monitor renal function. (See PRECAUTIONS, General and PRECAUTIONS, Geriatric Use.)

Impaired Renal Function

See PRECAUTIONS, General.

NOTE: As with antibiotic therapy in general, administration of cefotaxime should be continued for a minimum of 48 to 72 hours after the patient defervesces or after evidence of bacterial eradication has been obtained; a minimum of 10 days of treatment is recommended for infections caused by Group A beta-hemolytic streptococci in order to guard against the risk of rheumatic fever or glomerulonephritis; frequent bacteriologic and clinical appraisal is necessary during therapy of chronic urinary tract infection and may be required for several months after therapy has been completed; persistent infections may require treatment of several weeks and doses smaller than those indicated above should not be used.

Preparation of cefotaxime for injection sterile

Cefotaxime for IM or IV administration should be reconstituted as follows:

Strength | Diluent (mL) | Withdrawable Volume (mL) | Approximate Concentration (mg/mL)
500 mg vial* (IM) | 2 | 2.2 | 230
1 g vial* (IM) | 3 | 3.4 | 300
2 g vial* (IM) | 5 | 6.0 | 330
500 mg vial* (IV) | 10 | 10.2 | 50
1 g vial* (IV) | 10 | 10.4 | 95
2 g vial* (IV) | 10 | 11.0 | 180

(*) in conventional vials

Shake to dissolve; inspect for particulate matter and discoloration prior to use. Solutions of cefotaxime range from very pale yellow to light amber, depending on concentration, diluent used, and length and condition of storage.

For intramuscular use: Reconstitute VIALS with Sterile Water for Injection or Bacteriostatic Water for Injection as described above.

For intravenous use: Reconstitute VIALS with at least 10 mL of Sterile Water for Injection. Reconstitute INFUSION BOTTLES with 50 or 100 mL of 0.9% Sodium Chloride Injection or 5% Dextrose Injection. For other diluents, see COMPATIBILITY AND STABILITY section.

NOTE: Solutions of cefotaxime must not be admixed with aminoglycoside solutions. If cefotaxime and aminoglycosides are to be administered to the same patient, they must be administered separately and not as mixed injection.

A SOLUTION OF 1 G CEFOTAXIME IN 14 ML OF STERILE WATER FOR INJECTION IS ISOTONIC.

IM Administration: As with all IM preparations, cefotaxime should be injected well within the body of a relatively large muscle such as the upper outer quadrant of the buttock (i.e., gluteus maximus); aspiration is necessary to avoid inadvertent injection into a blood vessel. Individual IM doses of 2 grams may be given if the dose is divided and is administered in different intramuscular sites.

IV Administration: The IV route is preferable for patients with bacteremia, bacterial septicemia, peritonitis, meningitis, or other severe or life-threatening infections, or for patients who may be poor risks because of lowered resistance resulting from such debilitating conditions as malnutrition, trauma, surgery, diabetes, heart failure, or malignancy, particularly if shock is present or impending.

For intermittent IV administration, a solution containing 1 gram or 2 grams in 10 mL of Sterile Water for Injection can be injected over a period of three to five minutes. Cefotaxime should not be administered over a period of less than three minutes. (See WARNINGS). With an infusion system, it may also be given over a longer period of time through the tubing system by which the patient may be receiving other IV solutions. However, during infusion of the solution containing cefotaxime, it is advisable to discontinue temporarily the administration of other solutions at the same site.

For the administration of higher doses by continuous IV infusion, a solution of cefotaxime may be added to IV bottles containing the solutions discussed below.

Compatibility and Stability

Solutions of cefotaxime reconstituted as described above (Preparation of cefotaxime for injection sterile) remain chemically stable (potency remains above 90%) as follows when stored in original containers and disposable plastic syringes:

Strength | Reconstituted Concentration mg/mL | Stability at or below 22ºC | Stability under Refrigeration (at or below 5ºC)
Strength | Reconstituted Concentration mg/mL | Stability at or below 22ºC | Original Containers | Plastic Syringes
500 mg vial IM | 230 | 12 hours | 7 days | 5 days
1 g vial IM | 300 | 12 hours | 7 days | 5 days
2 g vial IM | 330 | 12 hours | 7 days | 5 days
500 mg vial IV | 50 | 24 hours | 7 days | 5 days
1 g vial IV | 95 | 24 hours | 7 days | 5 days
2 g vial IV | 180 | 12 hours | 7 days | 5 days

Reconstituted solutions stored in original containers and plastic syringes remain stable for 13 weeks frozen.

Reconstituted solutions may be further diluted up to 1000 mL with the following solutions and maintain satisfactory potency for 24 hours at or below 22°C, and at least 5 days under refrigeration (at or below 5°C): 0.9% Sodium Chloride Injection; 5 or 10% Dextrose Injection; 5% Dextrose and 0.9% Sodium Chloride Injection, 5% Dextrose and 0.45% Sodium Chloride Injection; 5% Dextrose and 0.2% Sodium Chloride Injection; Lactated Ringer's Solution; Sodium Lactate Injection (M/6); 10% Invert Sugar Injection, 8.5% TRAVASOL® (Amino Acid) Injection without Electrolytes.

NOTE: Cefotaxime solutions exhibit maximum stability in the pH 5-7 range. Solutions of cefotaxime should not be prepared with diluents having a pH above 7.5, such as Sodium Bicarbonate Injection.

Parenteral drug products should be inspected visually for particulate matter and discoloration prior to administration, whenever solution and container permit.

HOW SUPPLIED

Sterile Cefotaxime for Injection, USP, is a dry off-white to pale yellow crystalline powder supplied in vials and bottles containing cefotaxime sodium as follows:

500 mg cefotaxime (free acid equivalent) vials in packages of 10 (NDC 0143-9930-10)
1 g cefotaxime (free acid equivalent) vials in packages of 25 (NDC 0143-9931-25)
2 g cefotaxime (free acid equivalent) vials in packages of 25 (NDC 0143-9933-25)

NOTE: Cefotaxime for Injection, USP in the dry state should be stored at 20º to 25°C (68º to 77°F) [See USP Controlled Room Temperature].

The dry material as well as solutions tend to darken depending on storage conditions and should be protected from elevated temperatures and excessive light.

REFERENCES

1. Cockcroft, D.W. and Gault, M.H.: Prediction of Creatinine Clearance from Serum Creatinine, Nephron 16:31-41, 1976.

Travasol® is manufactured by Clintec.

Manufactured by:
HIKMA FARMACÊUTICA (PORTUGAL), S.A.
Estrada do Rio da Mó, 8, 8A e 8B – Fervença – 2705-906 Terrugem SNT, PORTUGAL

Distributed by:
Hikma Pharmaceuticals USA Inc.
Berkeley Heights, NJ 07922

Revised: June 2021
PIN105-WES/7

PRINCIPAL DISPLAY PANEL

NDC 0143-9930-01 Rx only
Cefotaxime
for Injection, USP
500 mg* per vial
For Intravenous or Intramuscular use

NDC 0143-9930-10 Rx only
Cefotaxime
for Injection, USP
500 mg* per vial
For Intravenous or Intramuscular use
10 x 500 mg vials

PRINCIPAL DISPLAY PANEL

NDC 0143-9931-01 Rx only
Cefotaxime
for Injection, USP
1 g* per vial
For Intravenous or Intramuscular use

NDC 0143-9931-25 Rx only
Cefotaxime
for Injection, USP
1 g* per vial
For Intravenous or Intramuscular use
25 x 1 g vials

PRINCIPAL DISPLAY PANEL

NDC 0143-9933-01
CEFOTAXIME
FOR INJECTION, USP
2 g*/vial
FOR IV OR IM USE
Rx ONLY